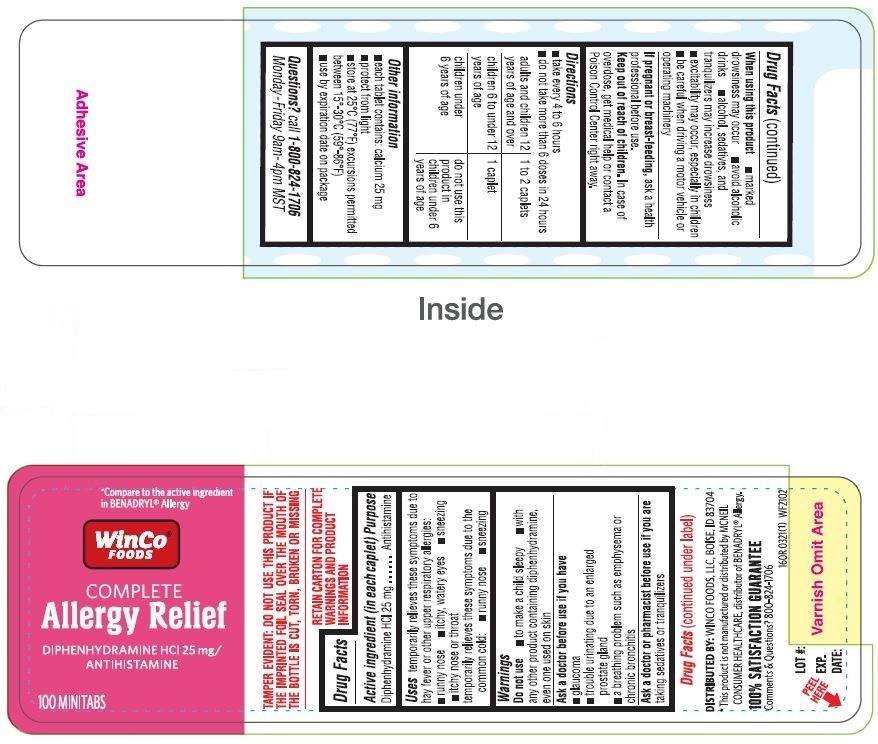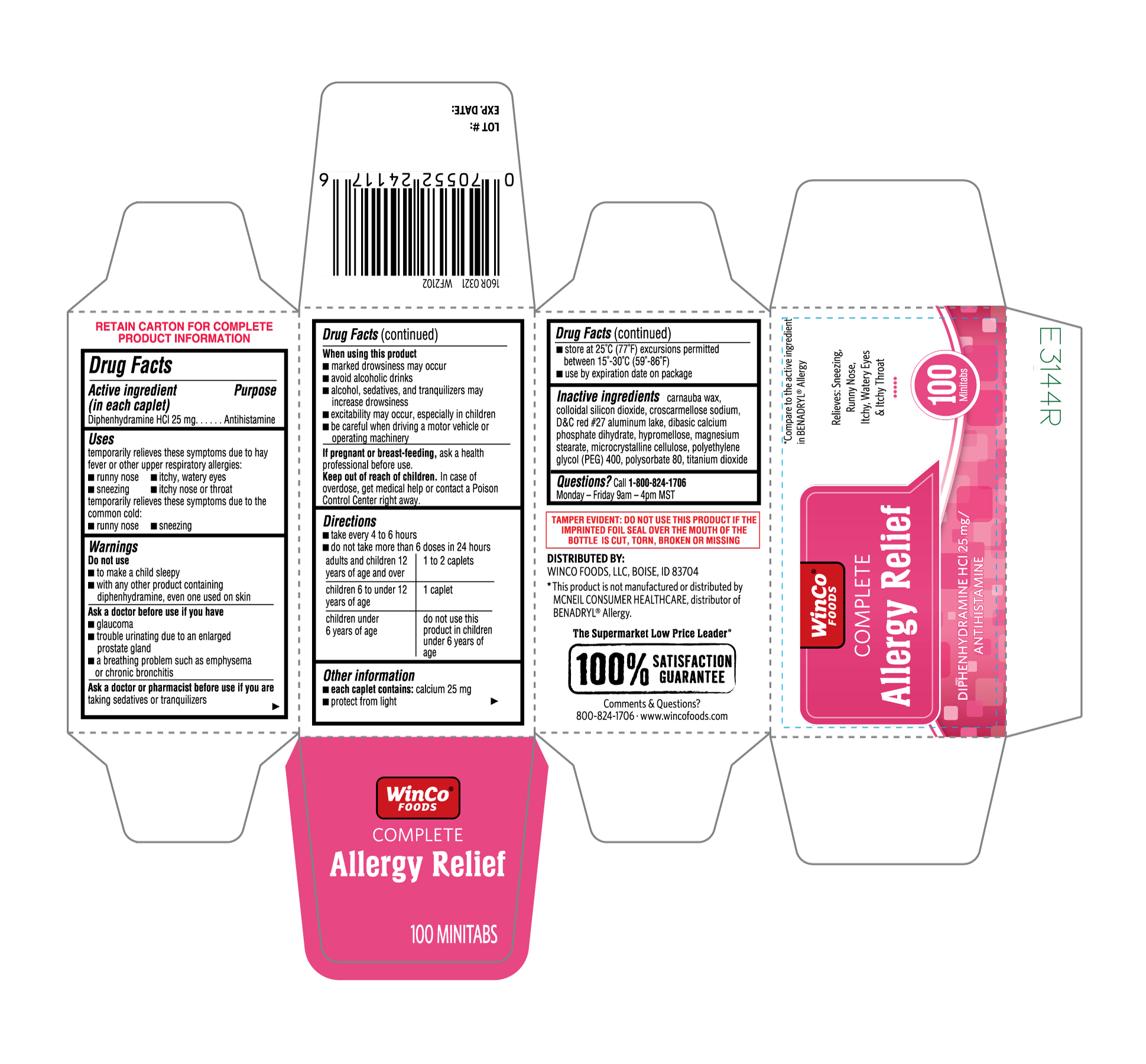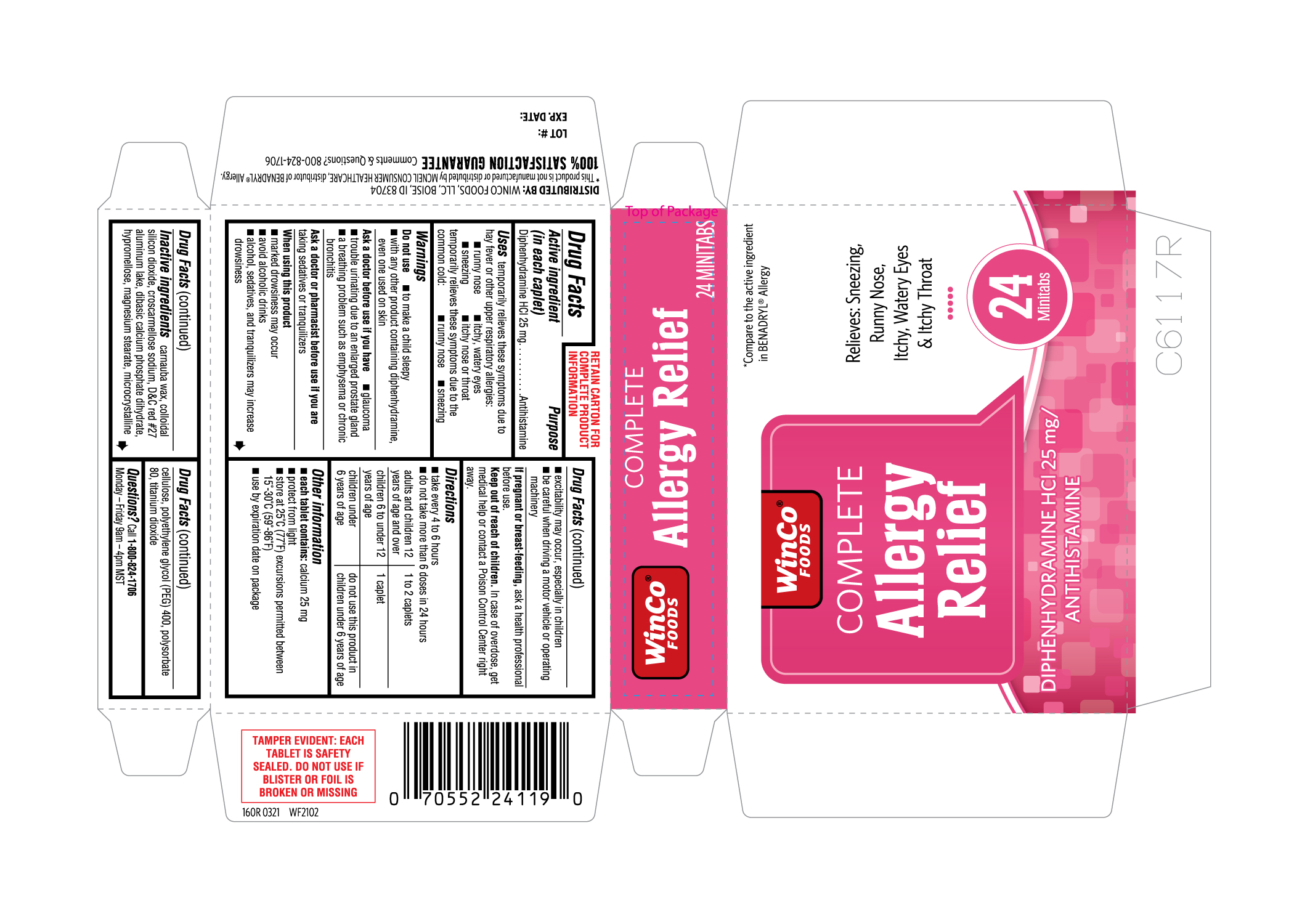 DRUG LABEL: Complete Allergy Relief
NDC: 67091-381 | Form: TABLET
Manufacturer: WinCo Foods LLC
Category: otc | Type: HUMAN OTC DRUG LABEL
Date: 20220106

ACTIVE INGREDIENTS: DIPHENHYDRAMINE HYDROCHLORIDE 25 mg/1 1
INACTIVE INGREDIENTS: CELLULOSE, MICROCRYSTALLINE; POLYETHYLENE GLYCOL 400; CARNAUBA WAX; SILICON DIOXIDE; CROSCARMELLOSE SODIUM; D&C RED NO. 27 ALUMINUM LAKE; DIBASIC CALCIUM PHOSPHATE DIHYDRATE; POLYSORBATE 80; TITANIUM DIOXIDE; MAGNESIUM STEARATE; HYPROMELLOSES

160R Winco Foods 67091 381 Diphenhydramine HCl 25 mg 24ct and 100ct

Active ingredients (in each caplet)
Diphenhydramine HCl 25 mg

Purpose
Antihistamine

Uses

temporarily relieves these symptoms due to hay fever or other upper respiratory allergies:
• runny nose
• itchy, watery eyes
• sneezing
• itchy nose or throat
temporarily relieves these symptoms due to the common cold:
• runny nose
• sneezing

Warnings

Do not use
• to make a child sleepy
• with any other product containing diphenhydramine, even one used on skin

Ask a doctor before use if you have
• glaucoma
• trouble urinating due to enlarged prostate gland
• a breathing problem such as emphysema or chronic bronchitis

Ask a doctor or pharmacist before use if you are taking sedatives or tranquilizers

When using this product
• marked drowsiness may occur
• avoid alcoholic drinks
• alcohol, sedatives, and tranquilizers may increase drowsiness
• excitability may occur, especially in children
• be careful when driving a motor vehicle or operating machinery

PREGNANCY OR BREAST FEEDING

If pregnant or breast-feeding, ask a health professional before use.

Keep out of reach of children. In case of overdose, get medical help or contact a Poison Control Center right away.

Directions
• take every 4 to 6 hours
• do not take more than 6 doses in 24 hours
adults and children 12 years of age and over: 1 to 2 caplets
children 6 to under 12 years of age: 1 caplet
children under 6 years of age: do not use this product in children under 6 years of age

Other information
• each caplet contains: calcium 25 mg
• protect from light
• store at 25°C (77° F) excursions permitted between 15°-30°C (59°-86°F)
• use by expiration date on package

INACTIVE INGREDIENT

Inactive ingredients carnauba wax, colloidal silicon dioxide, croscarmellose sodium, D&C red #27 aluminum lake, dibasic calcium phosphate dihydrate, hypromellose, magnesium stearate, microcrystalline cellulose, polyethylene glycol (PEG) 400, polysorbate 80, titanium dioxide

Questions? Call 1-800-824-1706

Monday - Friday 9 am-4pm MST